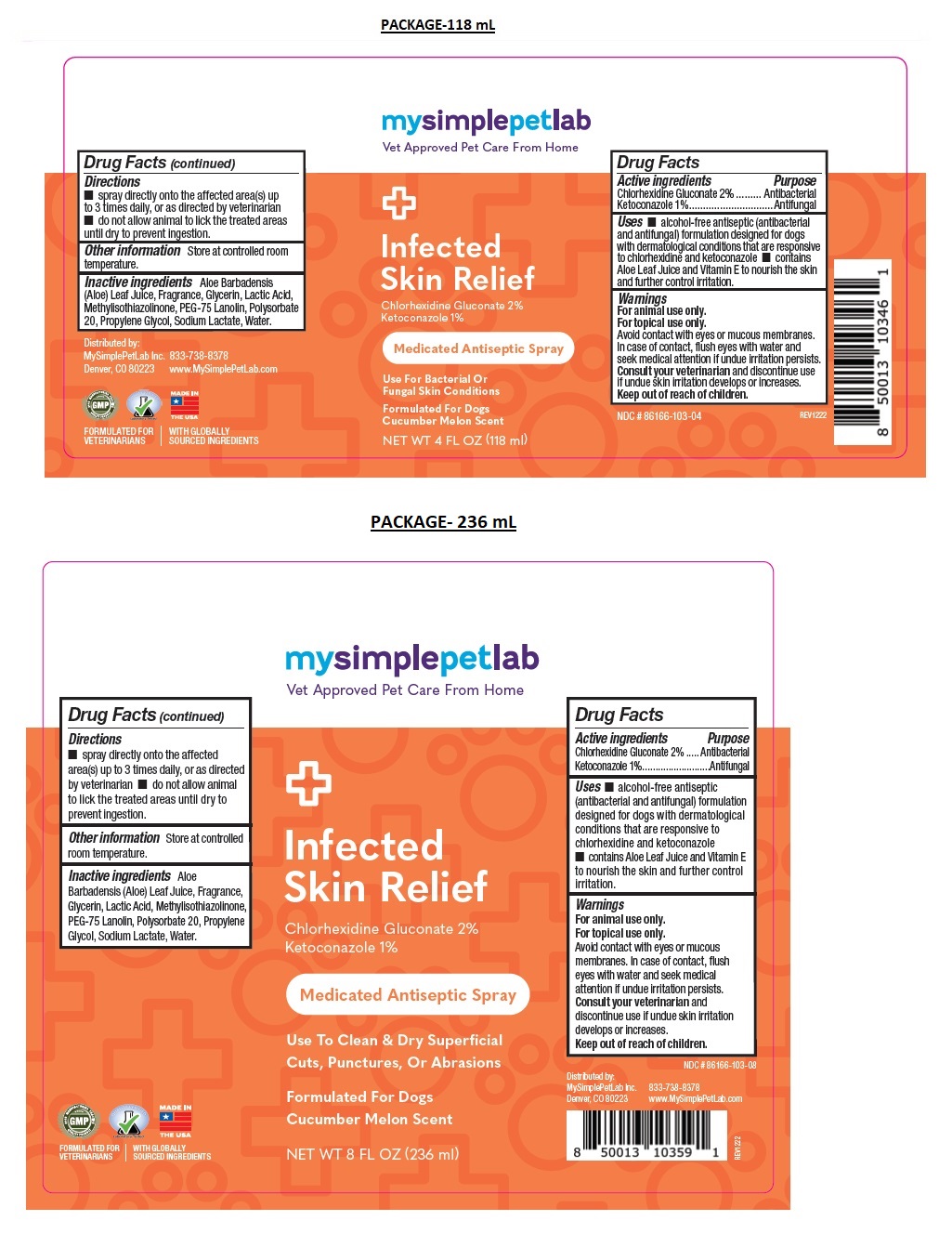 DRUG LABEL: MySimplePetLab Infected Skin Relief
NDC: 86166-103 | Form: SPRAY
Manufacturer: Mysimplepetlab Inc
Category: animal | Type: OTC ANIMAL DRUG LABEL
Date: 20230317

ACTIVE INGREDIENTS: CHLORHEXIDINE GLUCONATE 2 g/100 mL; KETOCONAZOLE 1 g/100 mL
INACTIVE INGREDIENTS: ALOE VERA LEAF; GLYCERIN; LACTIC ACID, UNSPECIFIED FORM; METHYLISOTHIAZOLINONE; PEG-75 LANOLIN; POLYSORBATE 20; PROPYLENE GLYCOL; SODIUM LACTATE; WATER

mysimplepetlab Infected Skin Relief

Active ingredients

Chlorhexidine Gluconate 2%
Ketoconazole 1%

Purpose

Antibacterial
Antifungal

Uses

• alcohol-free antiseptic (antibacterial and antifungal) formulation designed for dogs with dermatological conditions that are responsive to chlorhexidine and ketoconazole • contains Aloe Leaf Juice and Vitamin E to nourish the skin and further control irritation.

Warnings

For animal use only.
For topical use only.
Avoid contact with eyes or mucous membranes. In case of contact, flush eyes with water and seek medical attention if undue irritation persists.
Consult your veterinarian and discontinue use if undue skin irritation develops or increases.
Keep out of the reach of children.

Directions

• spray directly onto the affected area(s) up to 3 times daily, or as directed by veterinarian • do not allow animal to lick the treated areas until dry to
prevent ingestion.

Other information

Store at controlled room temperature.

Inactive ingredients

Aloe Barbadensis (Aloe) Leaf Juice, Fragrance, Glycerin, Lactic Acid, Methylisothiazolinone, PEG-75 Lanolin, Polysorbate 20, Propylene Glycol, Sodium Lactate, Water.

Vet Approved Pet Care From Home

Medicated Antiseptic Spray

Use For Bacterial Or Fungal Skin Conditions

Formulated For Dogs
Cucumber Melon Scent

FORMULATED FOR VETERINARIANS l WITH GLOBALLY SOURCED INGREDIENTS

MADE IN THE USA

Distributed by:
MySimplePetLab Inc.
Denver, CO 80223

833-738-8378
www.MySimplePetLab.com